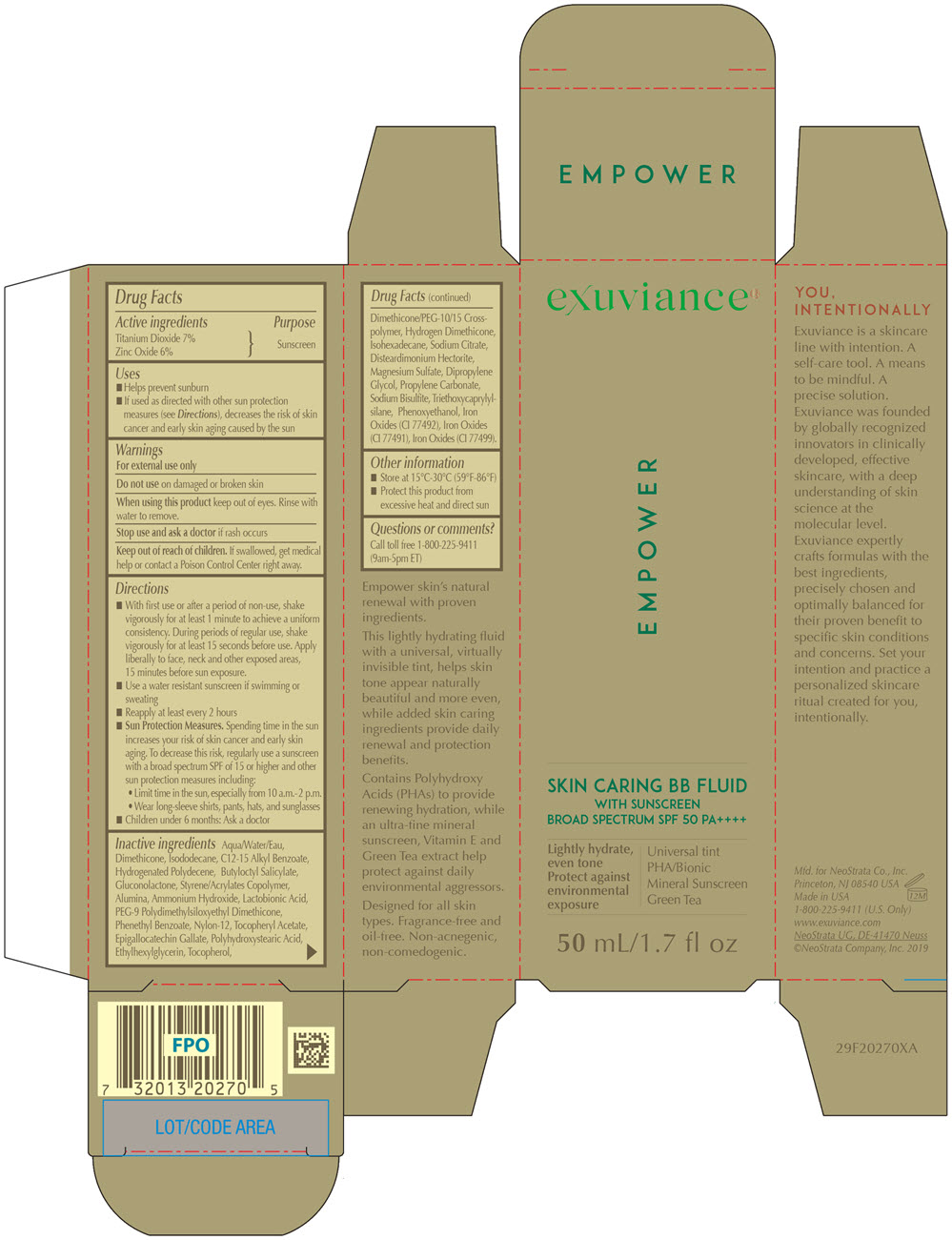 DRUG LABEL: Exuviance Skin Caring BB Fluid
NDC: 58414-0025 | Form: LOTION
Manufacturer: NeoStrata Company Inc.
Category: otc | Type: HUMAN OTC DRUG LABEL
Date: 20250110

ACTIVE INGREDIENTS: TITANIUM DIOXIDE 70 mg/1 mL; ZINC OXIDE 60 mg/1 mL
INACTIVE INGREDIENTS: WATER; DIMETHICONE; ISODODECANE; ALKYL (C12-15) BENZOATE; HYDROGENATED POLYDECENE TYPE I; BUTYLOCTYL SALICYLATE; GLUCONOLACTONE; ALUMINUM OXIDE; AMMONIA; LACTOBIONIC ACID; PEG-9 POLYDIMETHYLSILOXYETHYL DIMETHICONE; PHENETHYL BENZOATE; NYLON-12; .ALPHA.-TOCOPHEROL ACETATE; EPIGALLOCATECHIN GALLATE; POLYHYDROXYSTEARIC ACID (2300 MW); ETHYLHEXYLGLYCERIN; ISOHEXADECANE; TOCOPHEROL; DIMETHICONE/PEG-10/15 CROSSPOLYMER; HYDROGEN DIMETHICONE (13 CST); DIPROPYLENE GLYCOL; DISTEARDIMONIUM HECTORITE; MAGNESIUM SULFATE, UNSPECIFIED FORM; PROPYLENE CARBONATE; SODIUM CITRATE, UNSPECIFIED FORM; TRIETHOXYCAPRYLYLSILANE; SODIUM BISULFITE; PHENOXYETHANOL; FERRIC OXIDE RED; FERRIC OXIDE YELLOW; FERROSOFERRIC OXIDE

Exuviance®Skin Caring BB Fluid
with Sunscreen Broad Spectrum SPF 50

Drug Facts

Active ingredients

Titanium Dioxide 7%
Zinc Oxide 6%

Purpose

Sunscreen

Uses

- Helps prevent sunburn
- If used as directed with other sun protection measures (see Directions), decreases the risk of skin cancer and early skin aging caused by the sun

Warnings

For external use only

Do not useon damaged or broken skin

WHEN USING

When using this productkeep out of eyes. Rinse with water to remove.

Stop use and ask a doctorif rash occurs

Keep out of reach of children.If swallowed, get medical help or contact a Poison Control Center right away.

Directions

- With first use or after a period of non-use, shake vigorously for at least 1 minute to achieve a uniform consistency. During periods of regular use, shake vigorously for at least 15 seconds before use. Apply liberally to face, neck and other exposed areas, 15 minutes before sun exposure.
- Use a water resistant sunscreen if swimming or sweating
- Reapply at least every 2 hours
- Sun Protection Measures.Spending time in the sun increases your risk of skin cancer and early skin aging. To decrease this risk, regularly use a sunscreen with a broad spectrum SPF of 15 or higher and other sun protection measures including:
  - Limit time in the sun, especially from 10 a.m. – 2 p.m.
  - Wear long-sleeve shirts, pants, hats, and sunglasses
- Children under 6 months: Ask a doctor

Inactive ingredients

Water, Dimethicone, Isododecane, C12-15 Alkyl Benzoate, Hydrogenated Polydecene, Butyloctyl Salicylate, Gluconolactone, Styrene/Acrylates Copolymer, Alumina, Ammonium Hydroxide, Lactobionic Acid, PEG-9 Polydimethylsiloxyethyl Dimethicone, Phenethyl Benzoate, Nylon-12, Tocopheryl Acetate, Epigallocatechin Gallate, Polyhydroxystearic Acid, Ethylhexylglycerin, Tocopherol, Dimethicone/PEG-10/15 Crosspolymer, Hydrogen Dimethicone, Isohexadecane, Sodium Citrate, Disteardimonium Hectorite, Magnesium Sulfate, Dipropylene Glycol, Propylene Carbonate, Sodium Bisulfite, Triethoxycaprylylsilane, Phenoxyethanol, Iron Oxides (CI 77492), Iron Oxides (CI 77491), Iron Oxides (CI 77499).

Other information

- Store at 15°C-30°C (59°F – 86°F)
- Protect this product from excessive heat and direct sun

Questions or comments?

Call toll-free 1-800-225-9411 (9am – 5pm ET)

PRINCIPAL DISPLAY PANEL - 50 mL Bottle Carton

exuviance®

EMPOWER

SKIN CARING BB FLUID
WITH SUNSCREEN
BROAD SPECTRUM SPF 50 PA++++

Lightly hydrate,
even tone
Protect against
environmental
exposure
Universal tint
PHA/Bionic
Mineral Sunscreen
Green Tea

50 mL/1.7 fl oz